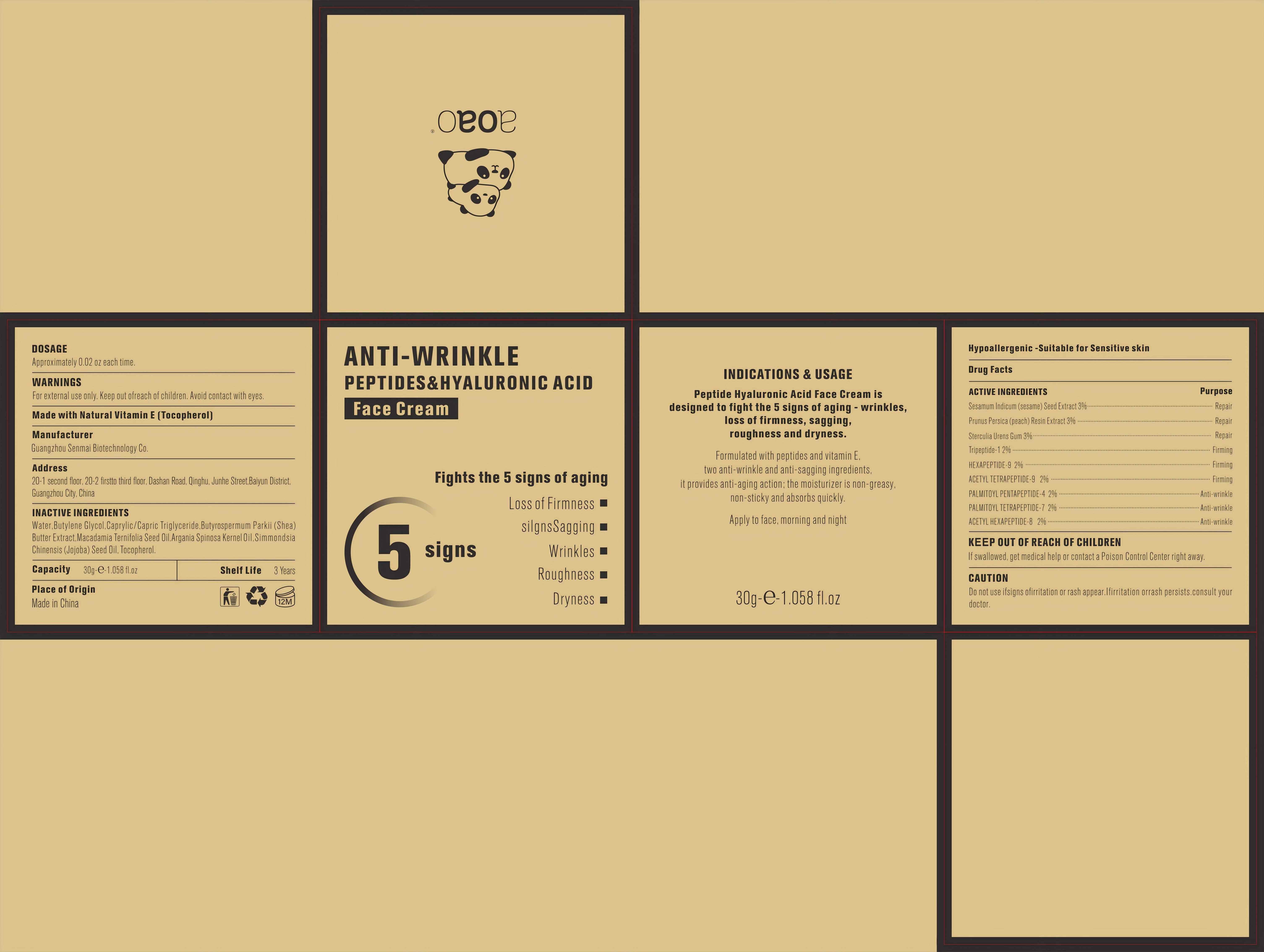 DRUG LABEL: Peptide Hyaluronic Acid Face Cream
NDC: 84509-008 | Form: CREAM
Manufacturer: Guangzhou Senmai Biotechnology Co.
Category: otc | Type: HUMAN OTC DRUG LABEL
Date: 20240808

ACTIVE INGREDIENTS: PALMITOYL PENTAPEPTIDE-4 600 mg/30 g; PALMITOYL TETRAPEPTIDE-7 600 mg/30 g; PREZATIDE 600 mg/30 g; ACETYL HEXAPEPTIDE-8 600 mg/30 g; STERCULIA URENS WHOLE 900 mg/30 g; SESAME SEED 900 mg/30 g; PEACH 900 mg/30 g; HEXAPEPTIDE-9 600 mg/30 g; ACETYL TETRAPEPTIDE-9 600 mg/30 g
INACTIVE INGREDIENTS: SHEA BUTTER; MEDIUM-CHAIN TRIGLYCERIDES; ARGAN OIL; JOJOBA OIL; BUTYLENE GLYCOL; TOCOPHEROL; MACADAMIA OIL; WATER

DOSAGE

Approximately 0.02 oz each time.

WARNINGS

For external use only. Keep out ofreach of children.Avoid contact with eyes.

DESCRIPTION

Made with Natural Vitamin E (Tocopherol)

Manufacturer

Guangzhou Senmai Biotechnology Co.

Address

20-1second floor, 20-2 first to third floor,Dashan Road,Qinghu,Junhe Street, Baiyun district, Guangzhou City, China.

Inactive Ingredients

Water,Butylene Glycol,Caprylic/Capric Triglyceride,Butyrospermum Parkii (Shea) Butter Extract,Macadamia Ternifolia Seed Oil,Argania Spinosa Kernel Oil,Simmondsia Chinensis (Jojoba) Seed Oil, Tocopherol.

Capacity

30g/1.058 Fl.oz

Shelf Life

3 Years

Place of Origin

Made in China

DESCRIPTION

Fights the 5 signs of aging
Loss of Firmness
silgnsSagging
Wrinkles
Roughness
Dryness

INDICATIONS & USAGE

Peptide Hyaluronic Acid Face Cream is designed to fight the 5 signs of aging - wrinkles, loss of firmness, sagging, roughness and dryness.
Formulated with peptides and vitamin E, two anti-wrinkle and anti-sagging ingredients, it provides anti-aging action; the moisturizer is non-greasy, non-sticky and absorbs quickly.
Apply to face, morning and night

DESCRIPTION

Hypoallergenic -Suitable for Sensitive skin

Active Ingredients

Sesamum Indicum (Sesame) Seed Extract 3%
Prunus Persica (Peach) Resin Extract 3%
Sterculia Urens Gum 3%
Tripeptide-1 2%
Hexapeptide-9 2%
Acetyl Tetrapeptide-9 2%
Palmitoyl Pentapeptide-4 2%

Palmitoyl Tetrapeptide-7 2%
Acetyl Hexapeptide-8 2%

Purpose

Repair,Firming,Anti-wrinkle.

Keep out of reach of children

If swallowed, get medical help or contact a Poison Control Center right away

CAUTION

Do not use ifsigns ofirritation or rash appear.Ifirritation orrash persists.consult your doctor.